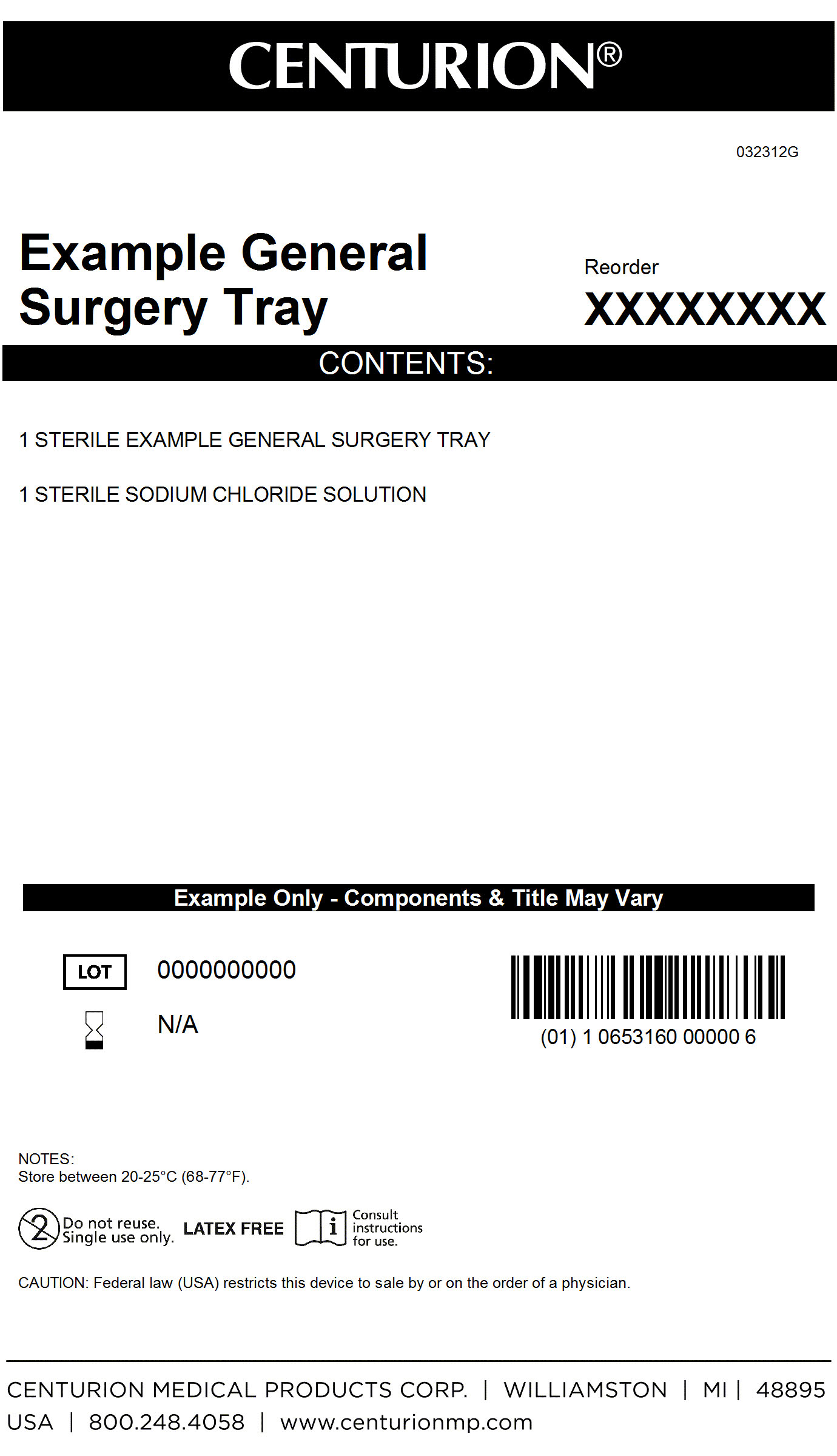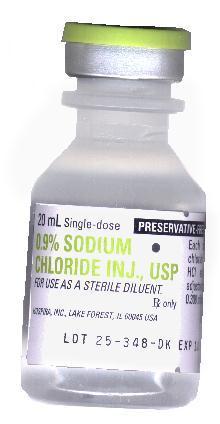 DRUG LABEL: General Surgery Kit
NDC: 24840-1534 | Form: KIT | Route: INTRAVENOUS
Manufacturer: Centurion Medical Products
Category: other | Type: MEDICAL DEVICE
Date: 20120926

ACTIVE INGREDIENTS: SODIUM CHLORIDE 9 mg/1 mL
INACTIVE INGREDIENTS: WATER; HYDROCHLORIC ACID; SODIUM HYDROXIDE

General Surgery Kit

DESCRIPTION

This preparation is designed solely for parenteral use only after addition of drugs that require dilution or must be dissolved in an aqueous vehicle prior to injection. 0.9% Sodium chloride injection, USP is a sterile, nonpyrogenic, isotonic solution of sodium chloride and water for injection. It contains no bacteriostat, antimicrobial agent or added buffer and is supplied only in single dose containers to dilute or dissolve drugs for injection. The solution may contain hydrochloric acid and/or sodium hydroxide for pH adjustment. pH is 5.3 (4.5 to 7.0). Sodium Chloride, USP is chemically designated NaCl, a white crystalline compound freely soluable in water.

PACKAGE LABEL

MM

General Surgery Kit Label

MM